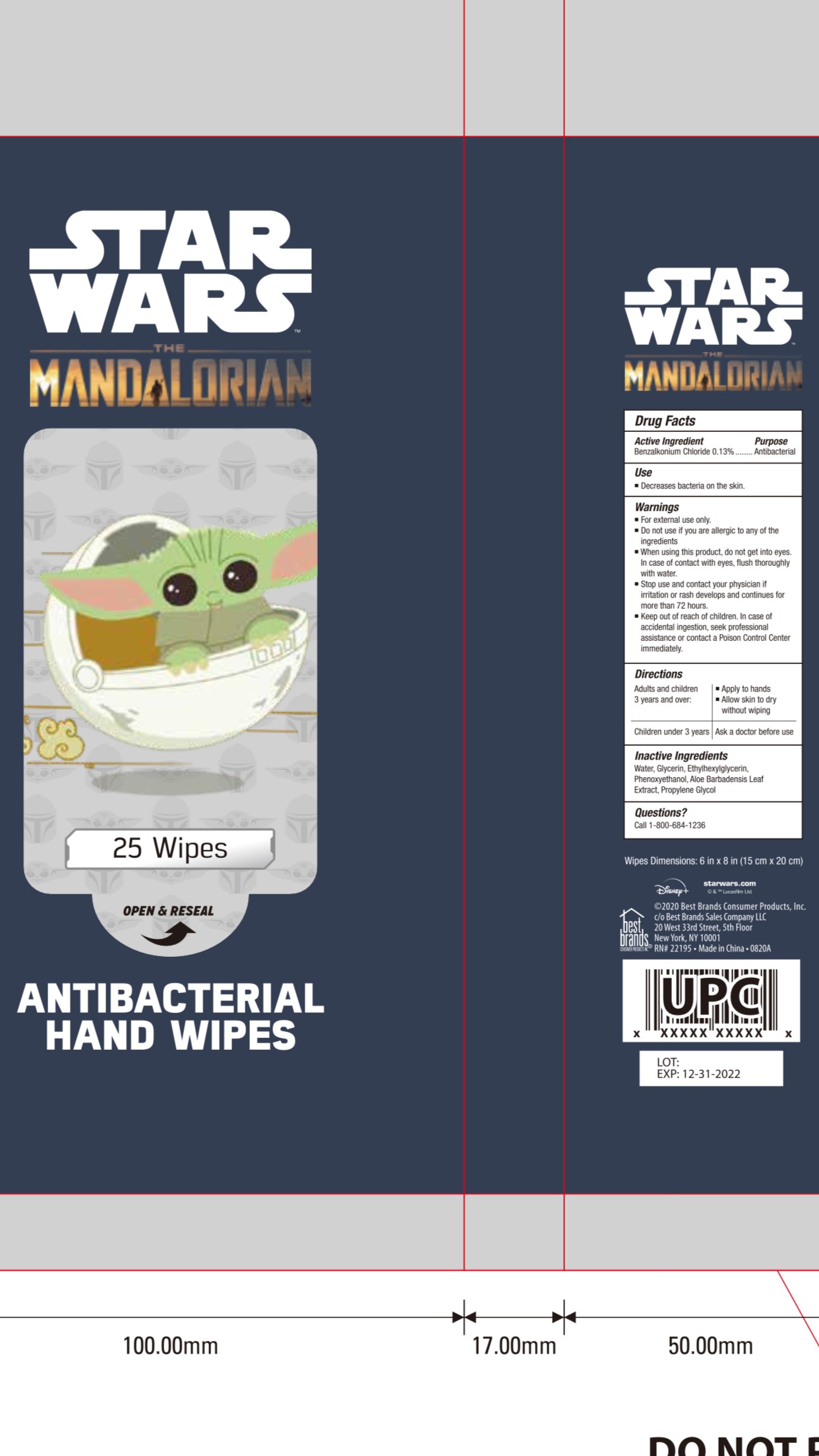 DRUG LABEL: STAR WARS The MANDALORIAN ANTIBACTERIAL HAND WIPES
NDC: 74530-052 | Form: SOLUTION
Manufacturer: Best Brand Consumers Products, Inc.
Category: otc | Type: HUMAN OTC DRUG LABEL
Date: 20201002

ACTIVE INGREDIENTS: BENZALKONIUM CHLORIDE 4.68 mg/1 1
INACTIVE INGREDIENTS: PHENOXYETHANOL; ETHYLHEXYLGLYCERIN; WATER; GLYCERIN; PROPYLENE GLYCOL; ALOE VERA LEAF

74530-052-Star Wars Hand Wipes/youquan

Active Ingredient(s)

Benzalkonium Chloride 0.13%

Purpose

Antibacterial

Use

Decrease the bacteria on the skin

Warnings

For external use only.

Do not use if you are allergic to any of the ingredients

When using this product, do not get into eyes. In case of contact with eyes, flush thoroughy with water

Stop use and contact your physician if irritation or rash develops and continues for more than 72 hours

Keep out of reach of children. In case of accidental ingestion, seek professional assitance or contact a Poison Control Center immediately.

Directions

Adults and children 3 years and over:

- Apply to hands
- Allow skin to dry without wiping

For children under 3 years

- Ask a doctor before use

Inactive ingredients

Water, glycerin, Ethylhexylglycerin, Phenoxyethanol, aloe barbadensis leaf extract, propylene glycol